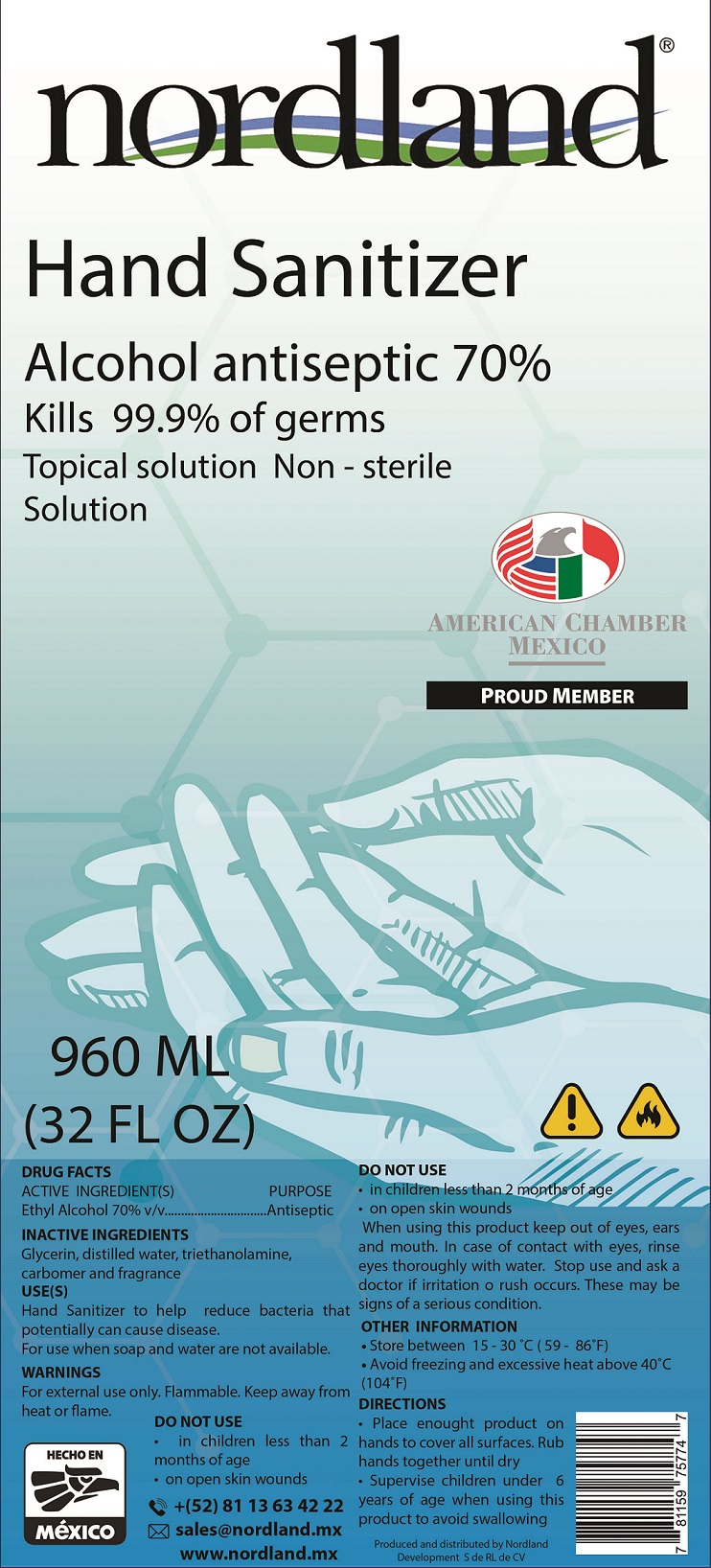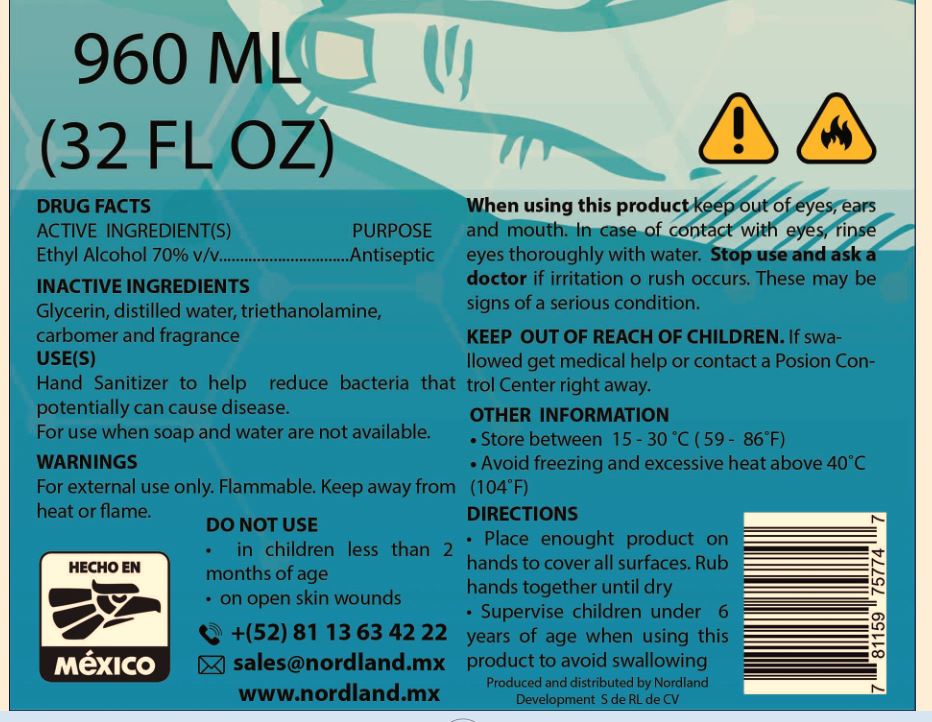 DRUG LABEL: Nordland Hand Sanitizer
NDC: 90029-003 | Form: GEL
Manufacturer: Nordland Development, S. de R.L. de C.V.
Category: otc | Type: HUMAN OTC DRUG LABEL
Date: 20201006

ACTIVE INGREDIENTS: ALCOHOL 0.7 mL/1 mL
INACTIVE INGREDIENTS: GLYCERIN; WATER; TROLAMINE; CARBOMER HOMOPOLYMER, UNSPECIFIED TYPE

Nordland Hand Sanitizer

ACTIVE INGREDIENTS

Ethyl Alcohol 70% v/v

PURPOSE

Antiseptic

INACTIVE INGREDIENTS

Glycerin, distilled water, triethanolamine, carbomer and fragrance

USE(S)

Hand Sanitizer to help reduce bacteria that potentially can cause disease.

For use when soap and water are not available.

KEEP OUT OF REACH OF CHILDREN.

If Swallowed get medical help or contact a Posion Control Center right away.

WARNINGS

For external use only. Flammable. Keep away from heat or flame.

DO NOT USE

- in children less than 2 months of age
- on open skin wounds

When using this product

keep out of eyes, ears and mouth. In case of contact with eyes, rinse eyes thoroughly with water.

Stop use and ask a doctor

if irritation or rush occurs. These may be signs of a seious condition.

OTHER INFORMATION

- Store between 15-30°C (59-86°F)
- Avoid freezing and excessive heat above 40°C (104°F)

DIRECTIONS

- Place enough product on hands to cover all surfaces. Rub hands together until dry
- Supervise children under 6 years of age when using this product to avoid swallowing